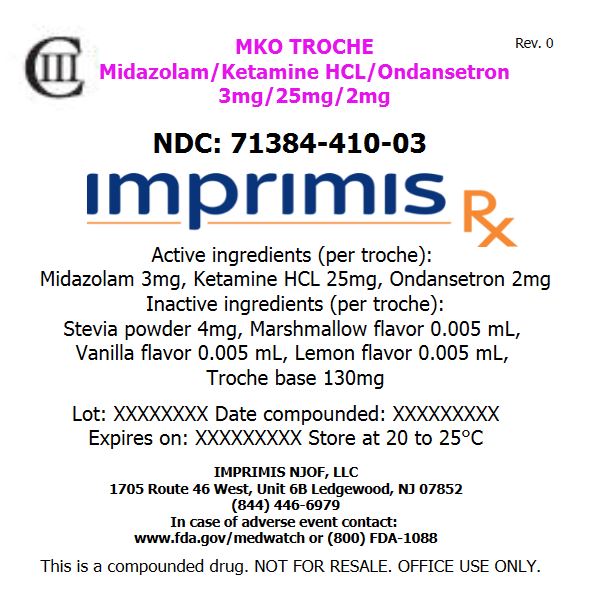 DRUG LABEL: MKO Melt Dose Pack
NDC: 71384-410 | Form: TROCHE
Manufacturer: Imprimis NJOF, LLC
Category: prescription | Type: HUMAN PRESCRIPTION DRUG LABEL
Date: 20190304
DEA Schedule: CIII

ACTIVE INGREDIENTS: MIDAZOLAM 3 mg/1 1; KETAMINE HYDROCHLORIDE 25 mg/1 1; ONDANSETRON HYDROCHLORIDE ANHYDROUS 2 mg/1 1

Storage and Handling

Store at 20° to 25° C (68° to 77° F)